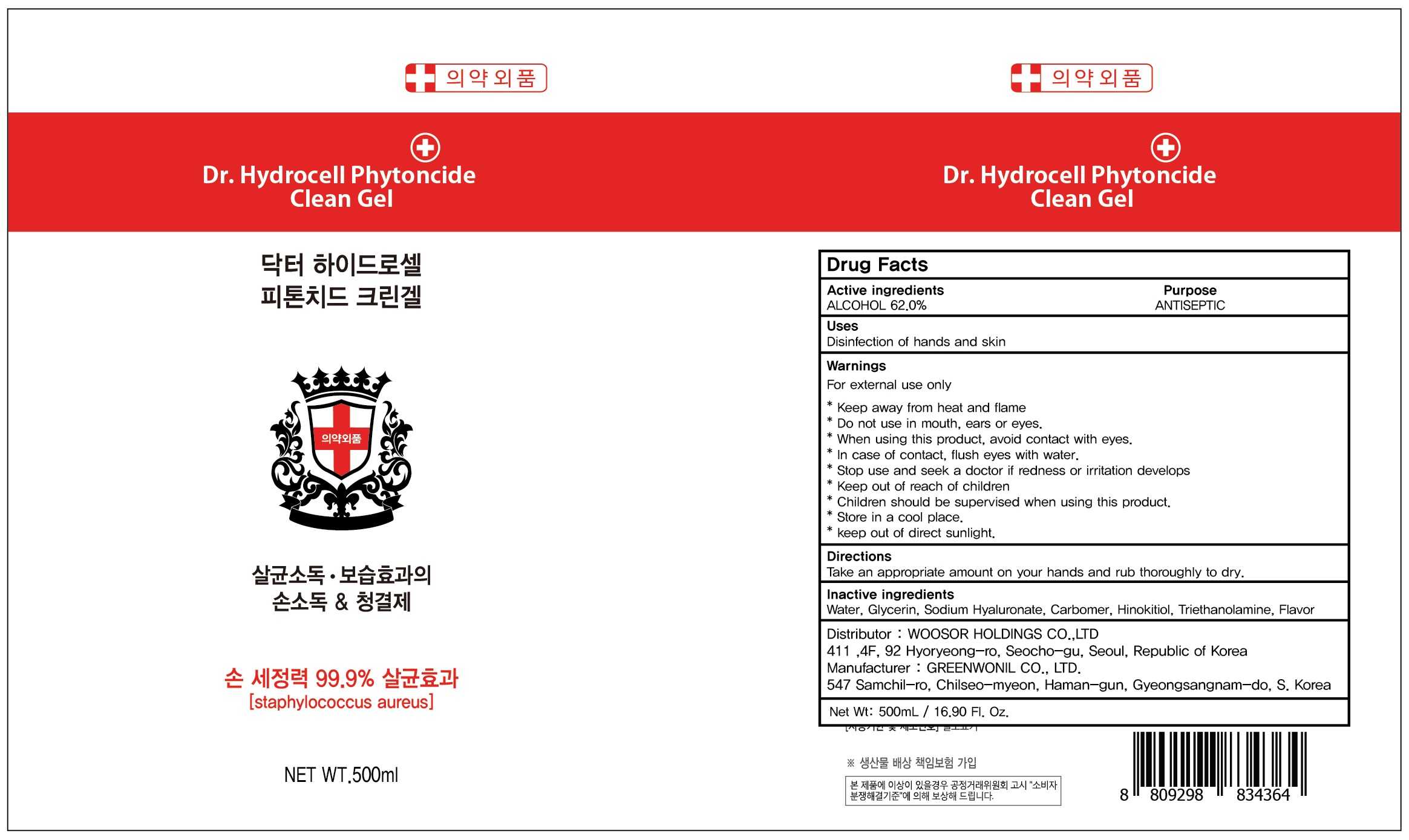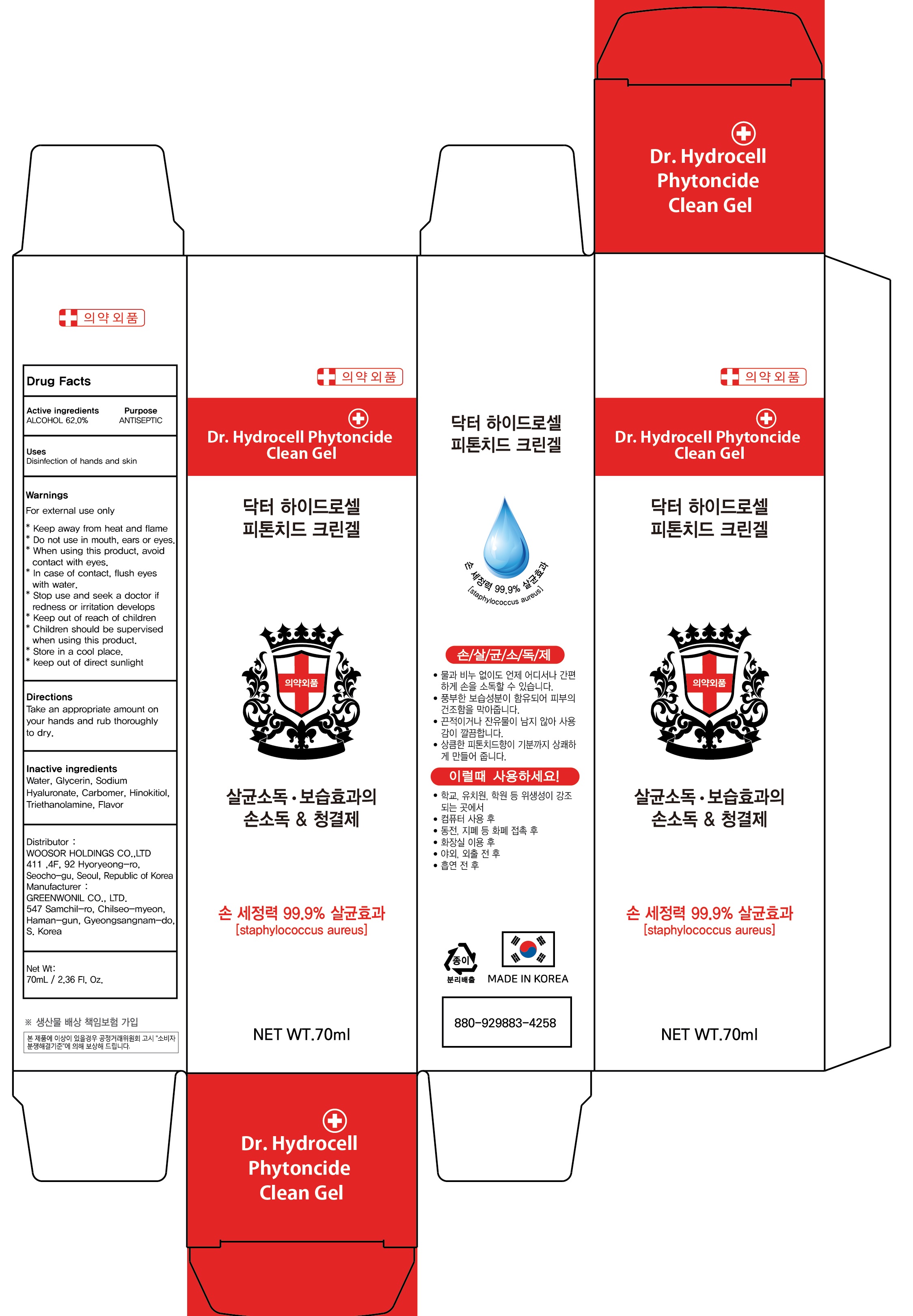 DRUG LABEL: DR Hydrocell Phytoncide Clean
NDC: 74922-010 | Form: GEL
Manufacturer: WOOSOR HOLDINGS CO., LTD
Category: otc | Type: HUMAN OTC DRUG LABEL
Date: 20200410

ACTIVE INGREDIENTS: ALCOHOL 62 g/100 mL
INACTIVE INGREDIENTS: Water; Glycerin; HYALURONATE SODIUM; CARBOMER HOMOPOLYMER, UNSPECIFIED TYPE; .BETA.-THUJAPLICIN; TROLAMINE

ACTIVE INGREDIENT

Active ingredients: ALCOHOL 62.0%

INACTIVE INGREDIENT

Inactive ingredients:

Water, Glycerin, Sodium Hyaluronate, Carbomer, Hinokitiol, Triethanolamine, Flavor

PURPOSE

Purpose: ANTISEPTIC

WARNINGS

For external use only

* Keep away from heat and flame
* Do not use in mouth, ears or eyes.
* When using this product, avoid contact with eyes.
* In case of contact, flush eyes with water.
* Stop use and seek a doctor if redness or irritation develops
* Keep out of reach of children
* Children should be supervised when using this product.
* Store in a cool place.
* keep out of direct sunlight.

KEEP OUT OF REACH OF CHILDREN

Uses

Disinfection of hands and skin

Directions

Take an appropriate amount on your hands and rub thoroughly to dry.